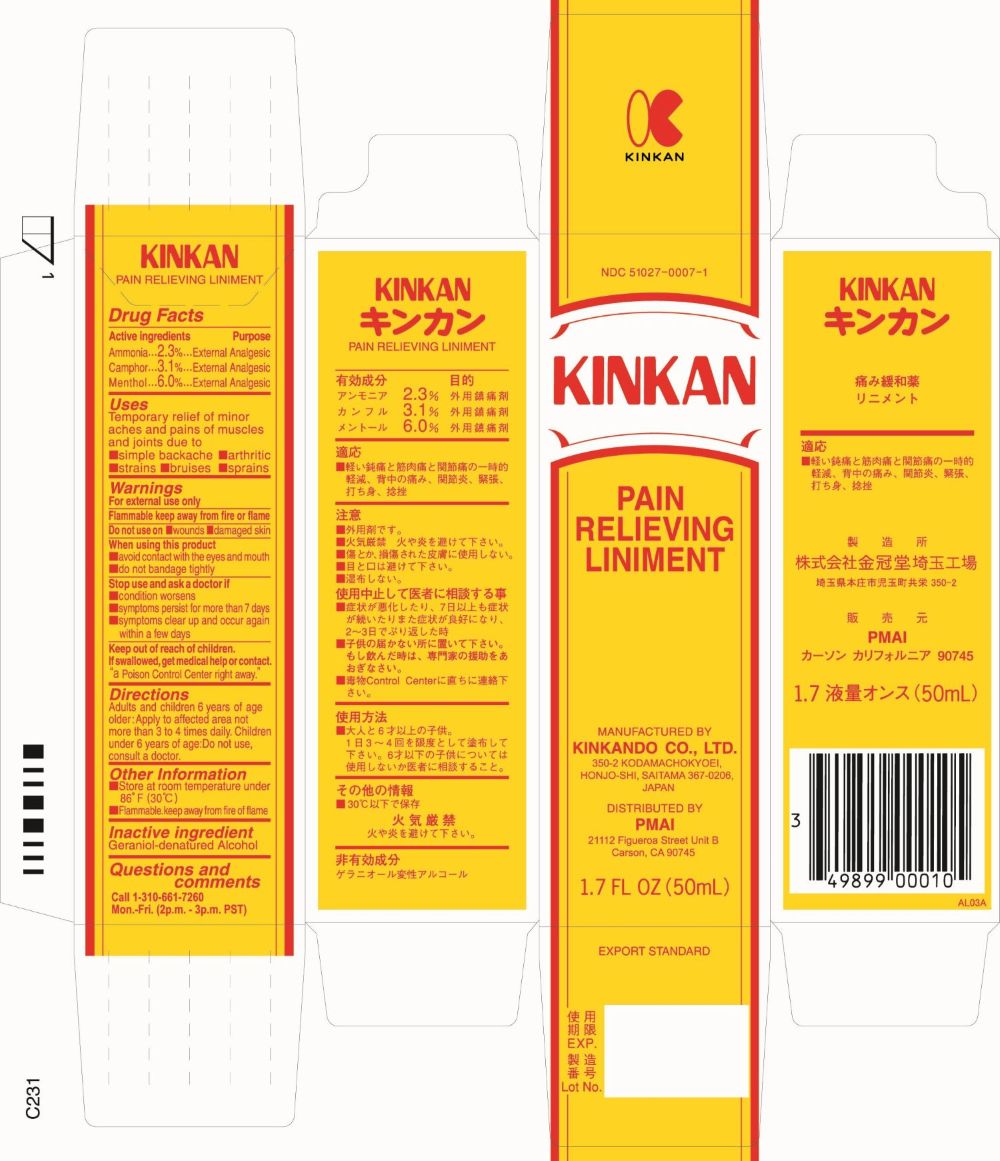 DRUG LABEL: KINKAN
NDC: 51027-0007 | Form: LINIMENT
Manufacturer: KINKANDO CO., LTD .
Category: otc | Type: HUMAN OTC DRUG LABEL
Date: 20251021

ACTIVE INGREDIENTS: AMMONIA 1.1 g/50 mL; CAMPHOR (NATURAL) 1.55 g/50 mL; MENTHOL 3 g/50 mL
INACTIVE INGREDIENTS: ALCOHOL

Drug Facts

Active ingredients

Ammonia 2.3%

Camphor 3.1%

Menthol 6.0%

Purpose

External Analgesic

External Analgesic

External Analgesic

Uses

Temporary relief of minor aches and pains of muscles and joints due to

- simple backache
- arthritic
- strains
- bruises
- sprains

Warnings

For external use only

Flammable keep away from fire or flame

Do not use on

- wounds
- damaged skin

When using this product

- avoid contact with the eyes and mouth
- do not bandage tightly

Stop use and ask a doctor if

- condition worsens
- symptoms persist for more than 7 days
- symptoms clear up and occur again within a few days

Keep out of reach of children.

If swallowed, get medical help or contact.“a Poison Control Center right away.”

Directions

Adults and children 6 years of age and older: Apply to affected area not more than 3 to 4 times daily. Children under 6 years of age: Do not use, consult a doctor.

Other Information

- Store at room temperature under 86°F (30°C)
- Flammable. keep away from fire or flame

Inactive ingredients

Geraniol-denatured Alcohol

Questions and comments

Call 1-310-661-7260 Mon.-Fri. (2p.m. - 3p.m. PST)

Principal Display Panel - 50 mL Bottle Label

NDC 51027-0007-1

KINKAN

PAIN
RELIEVING
LINIMENT

MANUFACTURED BY
KINKANDO CO., LTD.350-2 KODAMACHOKYOEI,
HONJO-SHI, SAITAMA 367-0206,
JAPAN

DISTRIBUTED BY
PMAI21112 Figueroa Street Unit B

Carson, CA 90745

1.7 FL OZ (50mL)